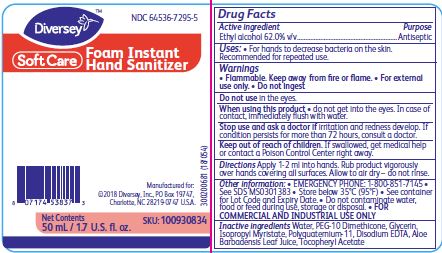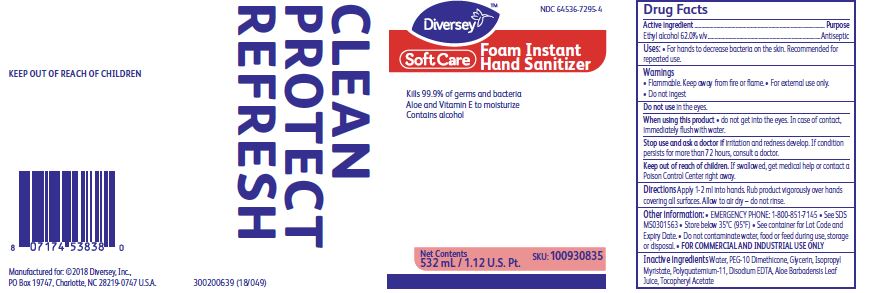 DRUG LABEL: Soft Care Foam Instant Hand Sanitizer
NDC: 64536-7295 | Form: LIQUID
Manufacturer: Diversey, Inc.
Category: otc | Type: HUMAN OTC DRUG LABEL
Date: 20241216

ACTIVE INGREDIENTS: ALCOHOL 62 mL/100 mL
INACTIVE INGREDIENTS: WATER; PEG-10 DIMETHICONE (600 CST); GLYCERIN; ISOPROPYL MYRISTATE; POLYQUATERNIUM-11 (1000000 MW); EDETATE DISODIUM; ALOE VERA LEAF; .ALPHA.-TOCOPHEROL ACETATE

Drug Facts

Active ingredient

Ethyl alcohol 62% v/v

Purpose

Antiseptic

Uses:

For hands to decrease bacteria on the skin.

Recommended for repeated use.

Warnings

Flammable. Keep away from fire or flame.

For external use only.

Do not ingest

Do not use in the eyes.

When using this product do not get into the eyes.

In case of contact, immediately flush with water.

Stop use and ask a doctor if irritation or redness develop.

If condition persists for more than 72 hours, consult a doctor.

Keep out of reach of children.

If swallowed, get medical help or contact a Poison Control Center right away.

Directions

Apply 1-2 ml into hands, rub product vigorously over hands covering all surfaces.

Allow to air dry - do not rinse.

Other information:

EMERGENCY PHONE: 1-800-851-7145

See SDS MS0301383

Store below 35 C (95 F)

See container for Lot Code and Expiry Date

Do not contaminate water, food or feed during use, storage or disposal.

For Commercial and Industrial Use Only

Inactive ingredients

Water, PEG-10 Dimethicone, Glycerin, Isopropyl Myristate, Polyquaternium-11, Disodium EDTA, Aloe Barbabensis Leaf Juice, Tocopheryl Acetate

PACKAGE LABEL

NDC 64536-7295-4

Diversey

SoftCare

Foam Instant

Hand Sanitizer

Kills 99.9% of germs and bacteria

Aloe and Vitamin E to moisturize

Contains alcohol

Clean

Protect

Refresh

Net Contents

532 mL/1.12 U.S. Pt.

SKU: 100930835